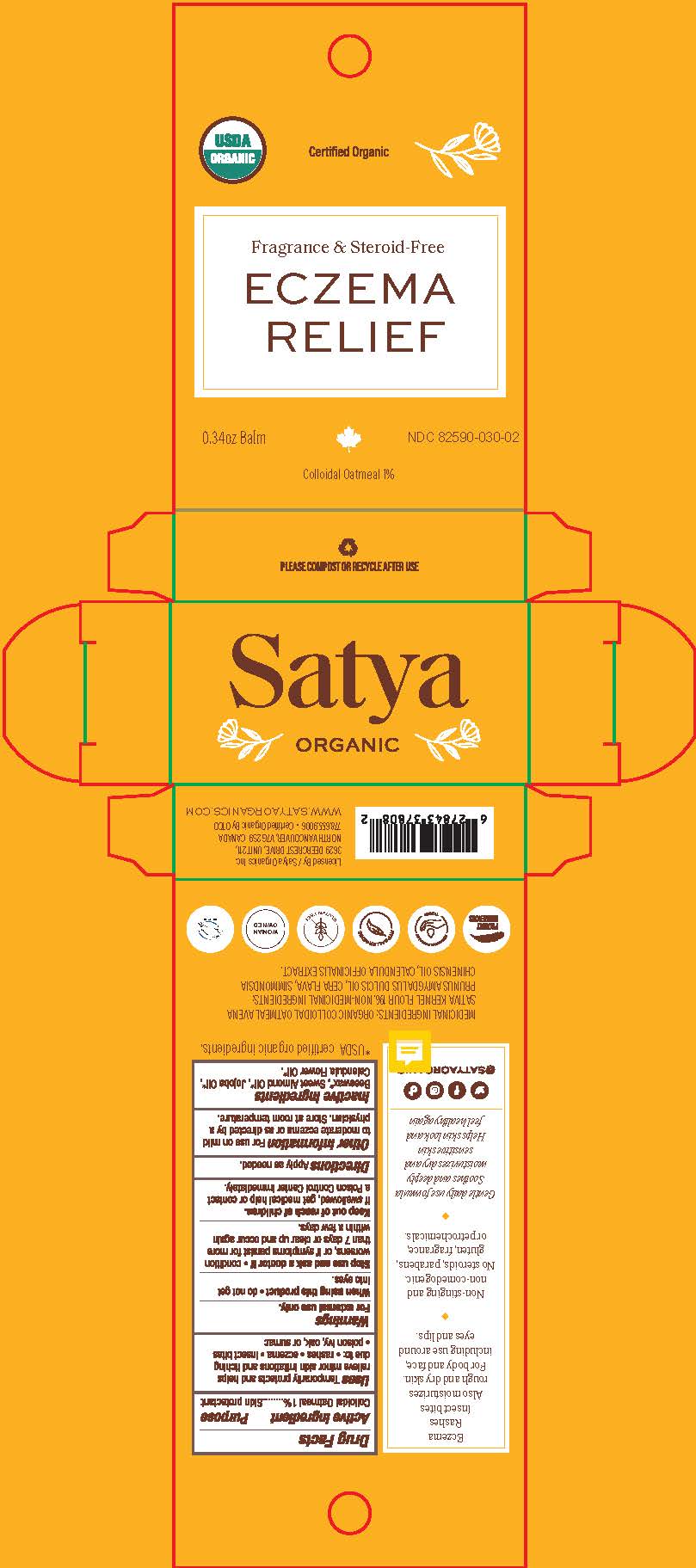 DRUG LABEL: Satya ORGANIC FRAGRANCE-FREE ECZEMA RELIEF
NDC: 82590-030 | Form: OINTMENT
Manufacturer: Satya Organic Inc.
Category: otc | Type: HUMAN OTC DRUG LABEL
Date: 20231004

ACTIVE INGREDIENTS: OATMEAL 10 mg/1 mL
INACTIVE INGREDIENTS: SYNTHETIC BEESWAX; CALENDULA OFFICINALIS FLOWER; JOJOBA OIL; ALMOND OIL

Satya ORGANIC FRAGRANCE-FREE ECZEMA RELIEF

Drug Facts

Active ingredient

Colloidal oatmeal 1%

Purpose

Skin protectant

Uses

temporarily protects and helps relieve minor skin irritation and itching due to:

• rashes • eczema • poison ivy, oak or sumac • insect bites

Warnings

For external use only.

When using this product do not get into eyes

Stop use and ask a doctor if

- condition worsens
- symptoms last more than 7 days or clear up and occur again within a few days

Keep out of reach of children. If swallowed, get medical help or contact a Poison Control Center right away.

Directions

apply as needed

INACTIVE INGREDIENT

Inactive ingredients Beeswax*, Calendula Flower Oil*, Jojoba Oil*, Sweet Almond Oil.*

* USDA certified organic ingredient.

Questions? 778.655.9006

@SATYAORGANIC

PACKAGE LABEL

Satya

ORGANIC

FRAGRANCE-FREE

ECZEMA

RELIEF

Skin Protectant Balm

Temporarily protects and helps relieve minor skin irritations and itching due to:

eczema ♦ rashes ♦ insect bites ♦ poison ivy, oat or sumac

Colloidal Oatmeal 1%

USDA Certified Organic NDC 82590-030-02

0.34 oz Balm